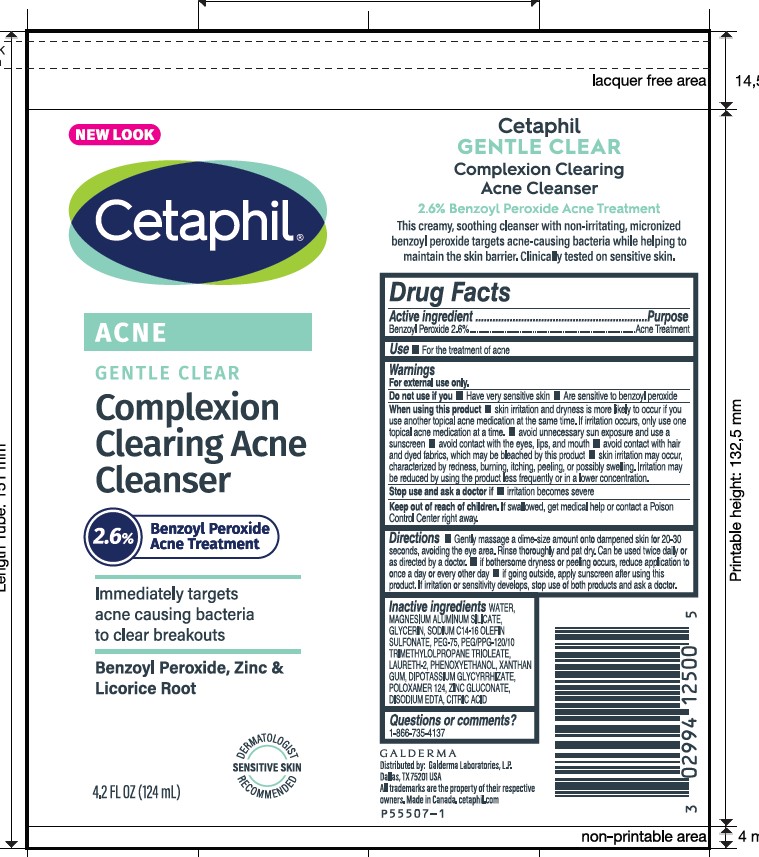 DRUG LABEL: Cetaphil Gentle Clear BPO Acne Cleanser
NDC: 0299-4125 | Form: CREAM
Manufacturer: Galderma Laboratories, L.P.
Category: otc | Type: HUMAN OTC DRUG LABEL
Date: 20231129

ACTIVE INGREDIENTS: Benzoyl Peroxide 2.6 g/100 mL
INACTIVE INGREDIENTS: Water; Magnesium Aluminum Silicate; Glycerin; Sodium C14-16 Olefin Sulfonate; Polyethylene Glycol 3350; Laureth-2; Phenoxyethanol; Xanthan Gum; Glycyrrhizinate Dipotassium; Poloxamer 124; Zinc Gluconate; Edetate Disodium; Citric Acid Monohydrate

Drug Facts

Active Ingredients

Benzoyl Peroxide 2.6%

Purpose

Acne treatment

Uses

For the treatment of acne

Warnings

For external use only.

Do not use if you
■ Have very sensitive skin
■ Are sensitive to benzoyl peroxide

When using this product
■ skin irritation and dryness is more likely to occur if you use another topical acne medication at the same time. If irritation occurs, only use one topical acne medication at a time. ■ avoid unnecessary sun exposure and use a sunscreen ■ avoid contact with the eyes, lips, and mouth ■ avoid contact with hair and dyed fabrics, which may be bleached by this product ■ skin irritation may occur, characterized by redness, burning, itching, peeling, or possibly swelling. Irritation may be reduced by using the product less frequently or in a lower concentration.

Stop use and ask a doctor if
■ Irritation becomes severe

Keep out of reach of children.
If swallowed, get medical help or contact a Poison Control Center right away.

Directions

■ Gently massage a dime-size amount onto dampened skin for 20 – 30 seconds, avoiding the eye area. Rinse thoroughly and pat dry. Can be used twice daily or as directed by a doctor. ■ If bothersome dryness or peeling occurs, reduce application to once a day or every other day. ■ If going outside, apply sunscreen after using this product. If irritation or sensitivity develops, stop use of both products and ask a doctor.

Inactive Ingredients

WATER, MAGNESIUM ALUMINUM SILICATE, GLYCERIN, SODIUM C14-16 OLEFIN SULFONATE, PEG-75,PEG/PPG-120/10 TRIMETHYLOLPROPANE TRIOLEATE, LAURETH-2, PHENOXYETHANOL, XANTHAN GUM, DIPOTASSIUM GLYCYRRHIZATE, POLOXAMER 124, ZINC GLUCONATE, DISODIUM EDTA, CITRIC ACID

Questions or comments?

1-866-735-4137

QUESTIONS

Distributed by:

Galderma Laboratories, L.P.

Dallas, TX 75201 USA

All trademarks are the property of their respective owners

Made in Canada

cetaphil.com.
P55507-1

Principle Display Panel - 4.2 FL OZ tube

NEW LOOK
Cetaphil®

ACNE
GENTLE CLEAR

Complexion
Clearing Acne
Cleanser
2.6 % Benzoyl Peroxide
Acne Treatment

Immediately targets
acne causing bacteria
to clear breakouts
Benzoyl Peroxide, Zinc &
Licorice Root
Dermatologist Recommended
Sensitive Skin
4.2 FL OZ (124 mL)